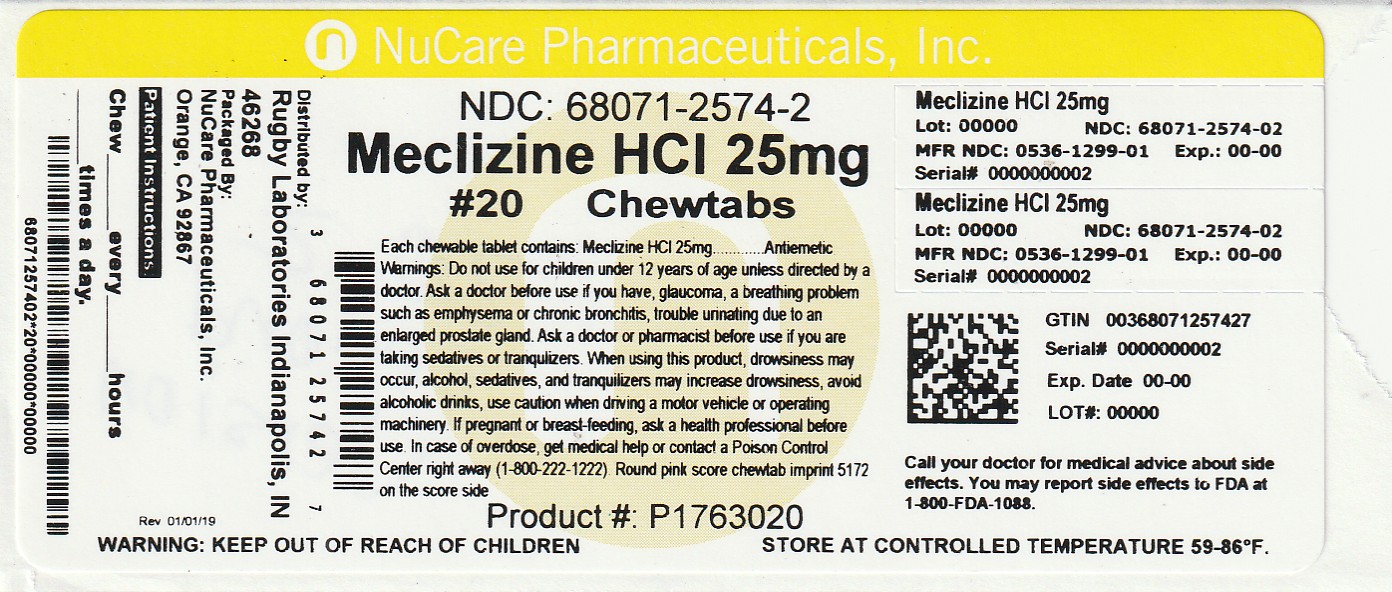 DRUG LABEL: Meclizine Hydrochloride
NDC: 68071-2574 | Form: TABLET, CHEWABLE
Manufacturer: NuCare Pharmaceuticals,Inc.
Category: otc | Type: HUMAN OTC DRUG LABEL
Date: 20260127

ACTIVE INGREDIENTS: MECLIZINE HYDROCHLORIDE 25 mg/1 1
INACTIVE INGREDIENTS: CROSPOVIDONE; VANILLA; MAGNESIUM STEARATE; RASPBERRY; STEARIC ACID; FD&C RED NO. 40; LACTOSE MONOHYDRATE; SACCHARIN SODIUM; CROSCARMELLOSE SODIUM; SILICON DIOXIDE

5172C- Rubgy

Drug Facts

Active ingredient (in each chewable tablet)
Meclizine HCl 25 mg

Purpose
Antiemetic

Uses

prevents and treats nausea, vomiting or dizziness due to motion sickness

WARNINGS

Do not use in

children under 12 years of age unless directed by a doctor

Ask a doctor before use if you have

 glaucoma

 a breathing problem such as emphysema or chronic bronchitis
 trouble urinating due to an enlarged prostate gland

Ask a doctor or pharmacist before use if

you are taking sedatives or tranquilizers

When using this product

 Do not exceed recommended dosage

 may cause drowsiness

 alcohol, sedatives, and tranquilizers may increase drowsiness

 avoid alcoholic drinks
 use caution when driving a motor vehicle or operating machinery

PREGNANCY OR BREAST FEEDING

If pregnant or breast-feeding, ask a health professional before use.

Keep out of reach of children.

OVERDOSAGE

In case of overdose, get medical help or contact a Poison Control Center right away (1-800-222-1222).

Directions

 Dosage should be taken one hour before travel starts

adults and children 12 years of age and over | chew 1 to 2 tablets once daily, or as directed by a doctor
children under 12 years of age | do not give this product to children under 12 years of age unless directed by a doctor

Other information

 Each tablet contains 0.09 mg of Magnesium and 0.82 mg of Sodium

 store at room temperature in a dry place

 keep lid tightly closed

INACTIVE INGREDIENT

Croscarmellose Sodium, Crospovidone, FD&C Red #40 Lake, French Vanilla Flavor, Lactose, Magnesium Stearate, Raspberry Flavor, Silica, Sodium Saccharin, Stearic Acid

Questions or comments?

1-800-645-2158

THIS PACKAGE FOR HOUSEHOLDS WITHOUT YOUNG CHILDREN

TAMPER EVIDENT: DO NOT USE IF IMPRINTED SAFETY SEAL UNDER CAP IS BROKEN OR MISSING

*This product is not manufactured or distributed by Prestige Brands, Inc owner of the registered trademark Bonine®.

Distributed by:
RUGBY® LABORATORIES
17177 N Laurel Park Dr., Suite 233
Livonia, MI 48152
www.rugbylaboratories.com